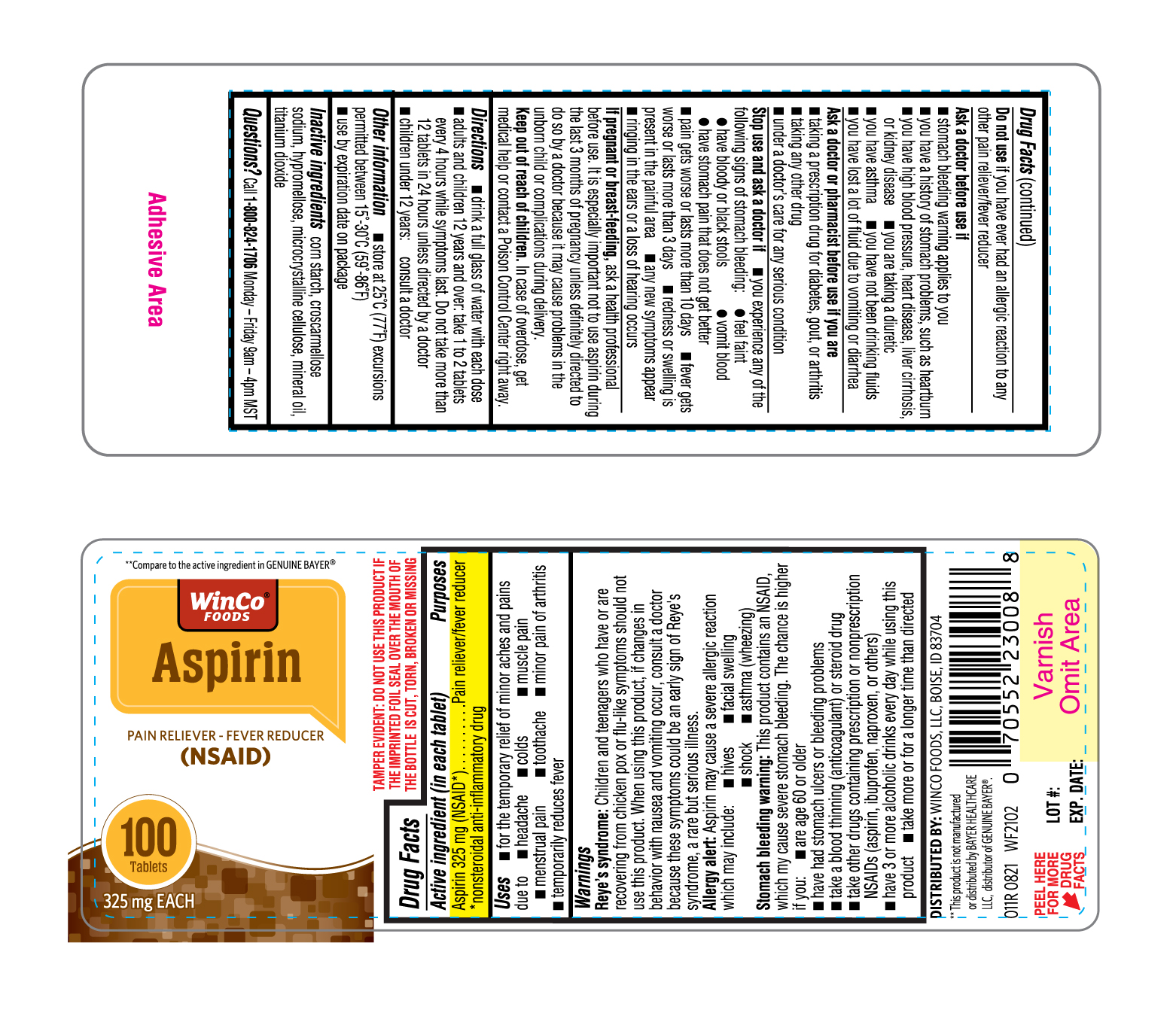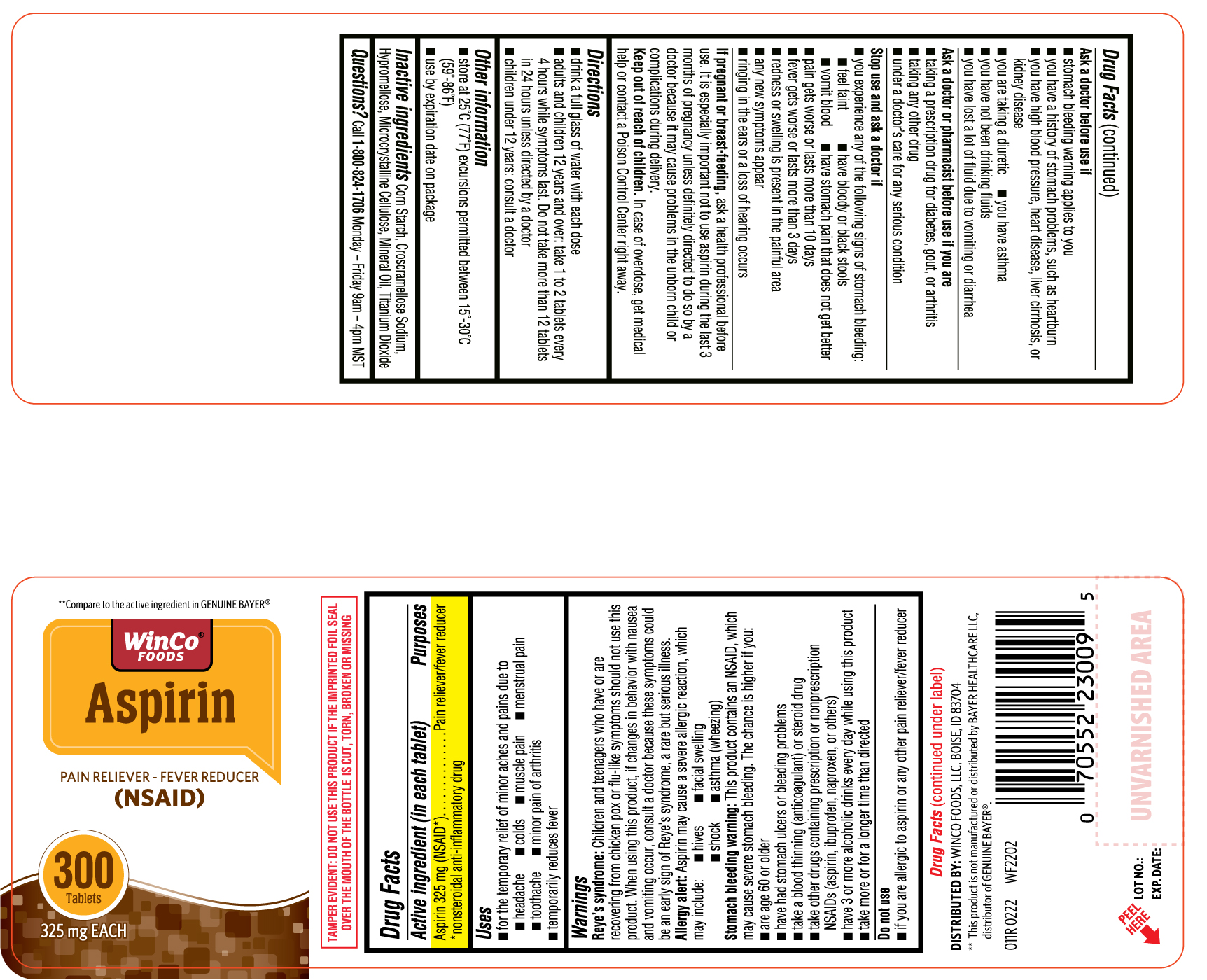 DRUG LABEL: Aspirin
NDC: 67091-382 | Form: TABLET
Manufacturer: WinCo Foods LLC
Category: otc | Type: HUMAN OTC DRUG LABEL
Date: 20220523

ACTIVE INGREDIENTS: ASPIRIN 325 mg/1 1
INACTIVE INGREDIENTS: STARCH, CORN; HYPROMELLOSES; MINERAL OIL; CELLULOSE, MICROCRYSTALLINE; TITANIUM DIOXIDE; CROSCARMELLOSE SODIUM

011R Winco Foods 67091 382 Aspirin tablet 325mg 100 ct and 300ct

Active ingredient (in each tablet)
Aspirin 325 mg (NSAID*)
*nonsteroidal anti-inflammatory drug

Purposes
Pain reliever/fever reducer

Uses
• for the temporary relief of minor aches and pains due to
o headache

o colds

o muscle pain
o menstrual pain

o toothache
o minor pain of arthritis
• temporarily reduces fever

Warnings
Reye’s syndrome: Children and teenagers who have or are recovering from chicken pox or flu-like symptoms should not use this product. When using this product, if changes in behavior with nausea and vomiting occur, consult a doctor because these symptoms could be an early sign of Reye’s syndrome, a rare but serious illness.
Allergy alert: Aspirin may cause a severe allergic reaction which may include:
• hives
• facial swelling
• shock
• asthma (wheezing)
Stomach bleeding warning: This product contains an NSAID, which may cause severe stomach bleeding. The chance is higher if you:
• are age 60 or older
• have had stomach ulcers or bleeding problems
• take a blood thinning (anticoagulant) or steroid drug
• take other drugs containing prescription or nonprescription NSAIDs (aspirin, ibuprofen, naproxen, or others)
• have 3 or more alcoholic drinks every day while using this product
• take more or for a longer time than directed

Do not use if you have ever had an allergic to Aspirin or any other pain reliever/fever reducer

Ask a doctor before use if
• stomach bleeding warning applies to you
• you have a history of stomach problems, such as heartburn
• you have high blood pressure, heart disease, liver cirrhosis, or kidney disease
• you are taking a diuretic
• you have asthma
• you have not been drinking fluids
• you have lost a lot of fluid due to vomiting or diarrhea

Ask a doctor or pharmacist before use if you are
• taking a prescription drug for diabetes, gout, or arthritis
• taking any other drug
• under a doctor’s care for any serious condition

Stop use and ask a doctor if
• you experience any of the following signs of stomach bleeding:
o feel faint
o have bloody or black stools

o vomit blood
o have stomach pain that does not get better
• pain gets worse or lasts more than 10 days
• fever gets worse or lasts more than 3 days
• redness or swelling is present in the painful area
• any new symptoms appear
• ringing in the ears or a loss of hearing occurs

PREGNANCY OR BREAST FEEDING

If pregnant or breast-feeding, ask a health professional before use. It is especially important not to use aspirin during the last 3 months of pregnancy unless definitely directed to do so by a doctor because it may cause problems in the unborn child or complications during delivery.

Keep out of reach of children. In case of overdose, get medical help or contact a Poison Control Center right away.

Directions
• drink a full glass of water with each dose
• adults and children 12 years and over: take 1 to 2 tablets every 4 hours while symptoms last. Do not take more than 12 tablets in 24 hours unless directed by a doctor
• children under 12 years: consult a doctor

Other information
• store at 25°C (77°F) excursions permitted between 15°-30°C (59°-86°F)
• use by expiration date on package

INACTIVE INGREDIENT

Inactive ingredients corn starch, croscarmellose sodium, hypromellose, microcrystalline cellulose, mineral oil, titanium dioxide

QUESTIONS

Questions? Call 1-800-824-1706 Monday – Friday 9am – 4pm MST